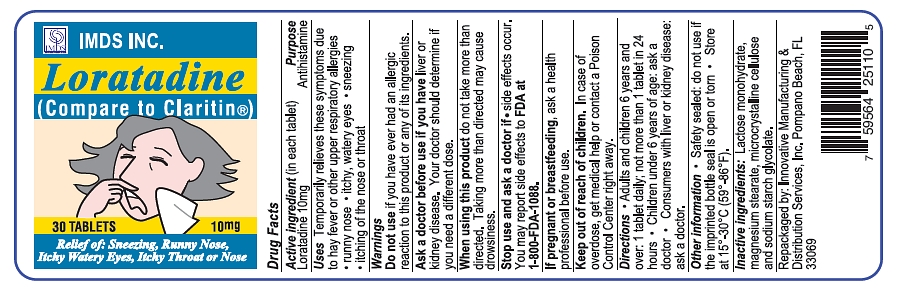 DRUG LABEL: Loratadine
NDC: 59564-251 | Form: TABLET
Manufacturer: Innovative Manufacturing and Distribution Services, Inc.
Category: otc | Type: HUMAN OTC DRUG LABEL
Date: 20100806

ACTIVE INGREDIENTS: LORATADINE 10 mg/1 1
INACTIVE INGREDIENTS: LACTOSE MONOHYDRATE; MAGNESIUM STEARATE; CELLULOSE, MICROCRYSTALLINE; SODIUM STARCH GLYCOLATE TYPE A POTATO

Drug Facts

Active ingredient

Loratadine 10mg

Purpose

Antihistamine

Uses

Temporarily relieves these symptoms due to hay fever or other upper respiratory allergies

- runny nose
- itchy, watery eyes
- sneezing
- itching of the nose or throat

Warnings

Do not use

if you have ever had an allergic reaction to this product or any of its ingredients.

Ask a doctor before use if you have

liver or kidney disease. Your doctor should determine if you need a different dose.

When using this product

do not take more than directed. Taking more than directed may cause drowsiness.

Stop use and ask a doctor if

- side effects occur.

You may report side effects to FDA at 1-800-FDA-1088.

If pregnant or breastfeeding

ask a health professional before use.

Keep out of reach of children.

In case of overdose, get medical help or contact a Poison Control Center right away.

Directions

- Adults and children 6 years and over: 1 tablet daily; not more than 1 tablet in 24 hours
- Children under 6 years of age: ask a doctor
- Consumers with liver or kidney disease: ask a doctor.

Other information

- Safety sealed: do not use if the imprinted bottle seal is open or torn
- Store at 15° - 30° C (59° - 86° F).

Inactive ingredients

Lactose monohydrate, magnesium stearate, microcrystalline cellulose and sodium starch glycolate.

Package/Label Principal Display Panel

IMDS INC.

Loratadine

(Compare to Claritin®)

30 TABLETS

10 mg

Relief of: Sneezing, Runny Nose,

Itchy Watery Eyes, Itchy Throat or Nose